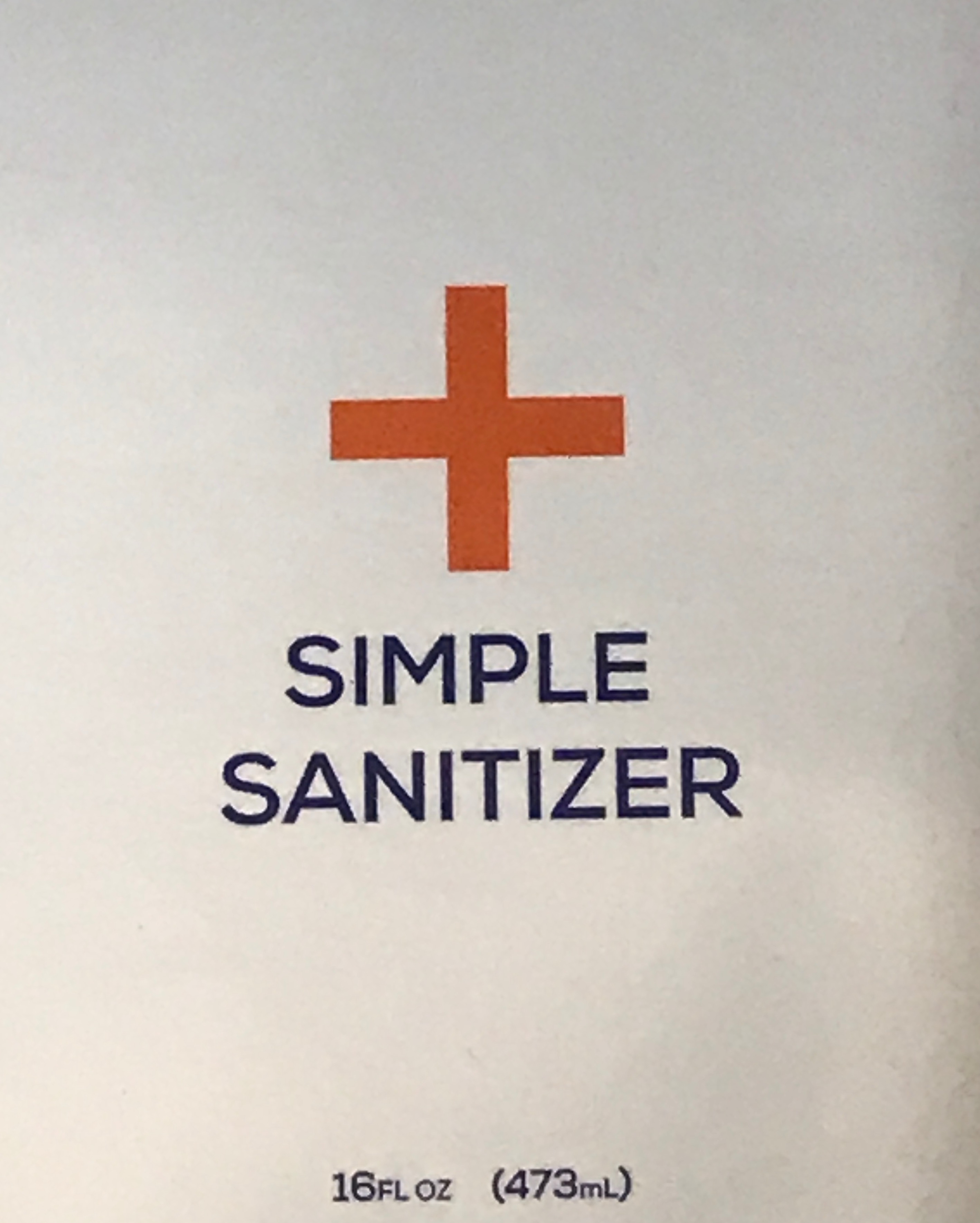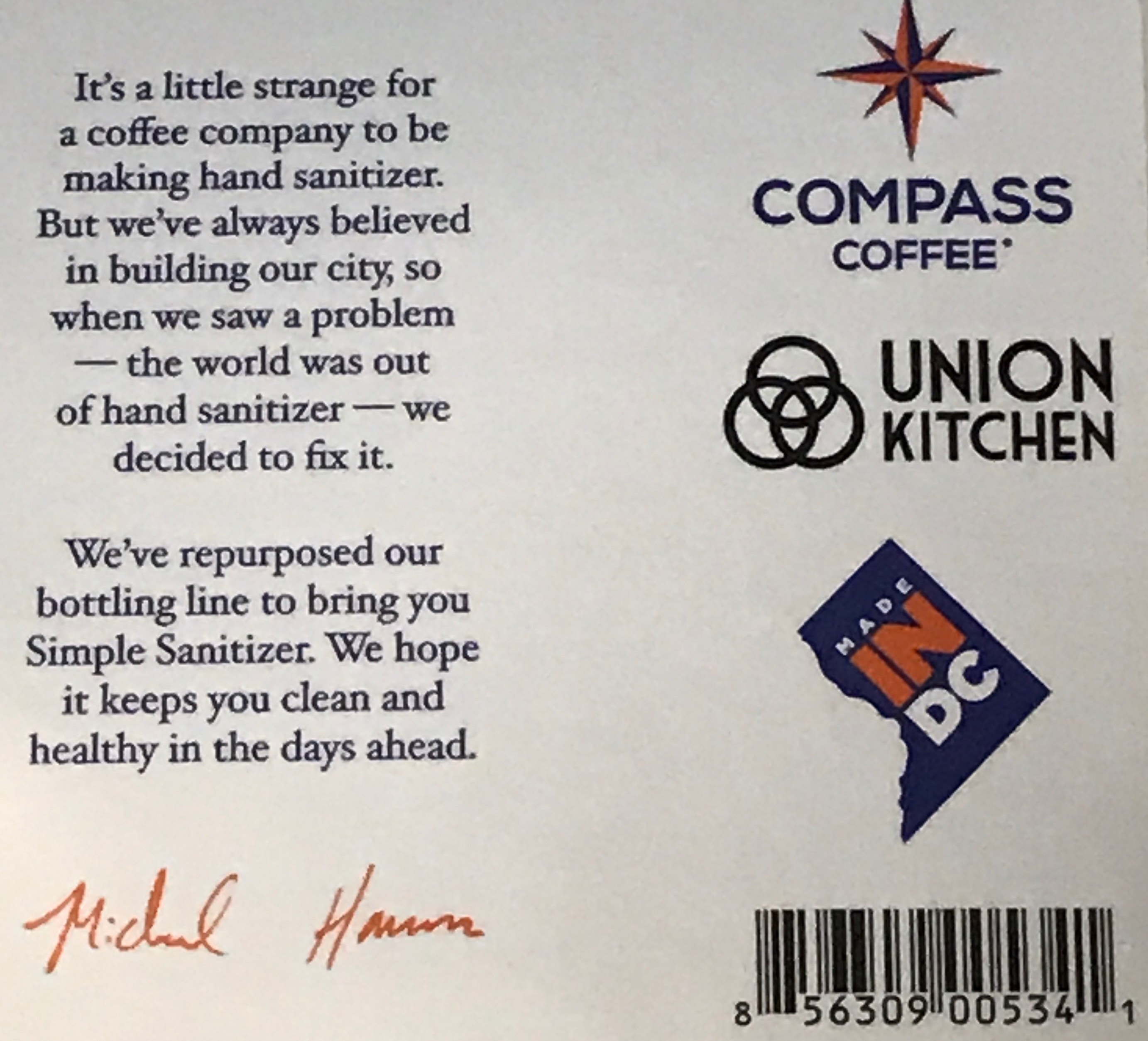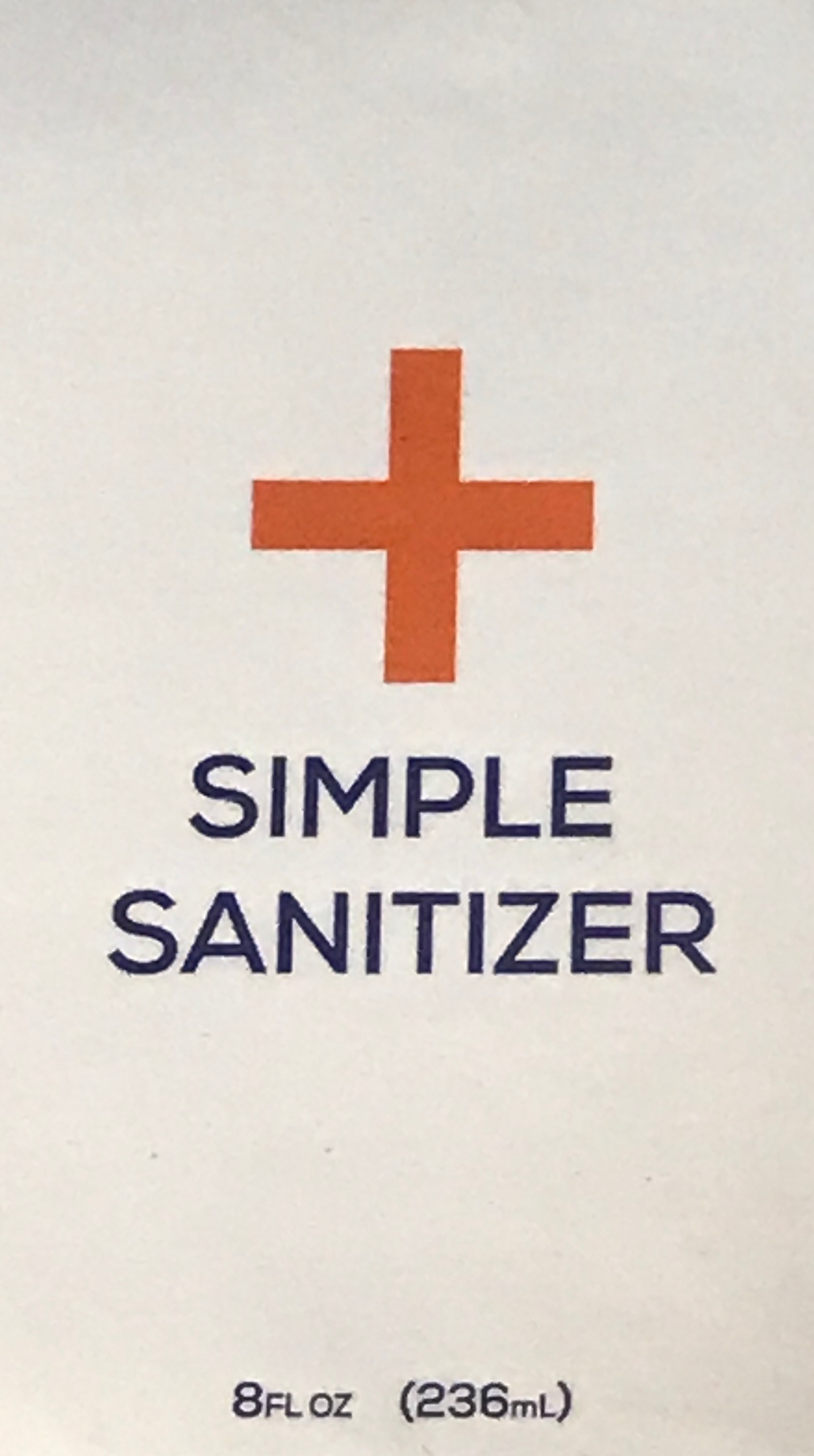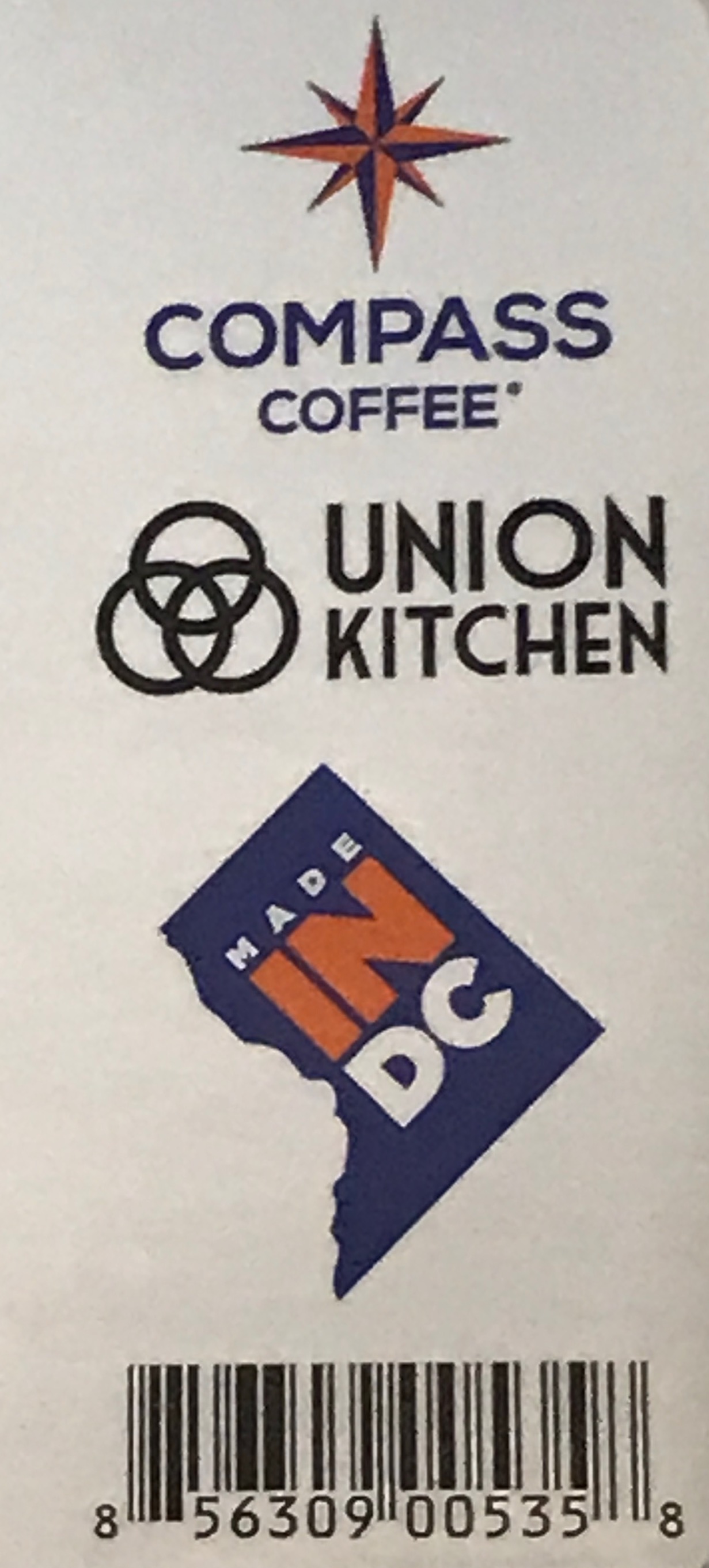 DRUG LABEL: Simple Sanitizer
NDC: 75333-002 | Form: GEL
Manufacturer: Compass Coffee Llc
Category: otc | Type: HUMAN OTC DRUG LABEL
Date: 20200505

ACTIVE INGREDIENTS: ISOPROPYL ALCOHOL 70 mL/100 mL
INACTIVE INGREDIENTS: HYDROGEN PEROXIDE 0.4 mL/100 mL; WATER 26 mL/100 mL; GLYCERIN 0.725 mL/100 mL; ALOE VERA LEAF 0.725 mL/100 mL; EUCALYPTUS OIL 0.1 mL/100 mL; 2,4,5-T-TROLAMINE 0.2 mL/100 mL; CARBOMER 940 0.3 mL/100 mL

Formula II

This is a hand sanitizer manufactured according to the Temporary Policy for Preparation of Certain Alcohol-Based Hand Sanitizer Products During the Public Health Emergency (CoViD-19); Guidance for Industry. The hand sanitizer is manufactured consistent with World Health Organization (WHO) formulation II.

Active Ingredient(s)

Isopropyl Alcohol 70% v/v. Purpose: Antimicrobial

Purpose

Antimicrobial

Use

Hand Sanitizer to help reduce bacteria on the skin.

Warnings

Flammable. Keep away from fire or flame. This product is intended for external use only.

When using this product, do not use in or near the eyes. In case of contact, rinse thoroughly with water.

Discontinue Use

Discontinue use if irritation or redness develops. If condition persists for more than 72 hours consult a doctor.

Keep out of reach of children. If swallowed, get medical help or contact a Poison Control Center right away.

Directions

- Place enough product in your palm to thoroughly cover your hands.
- Rub hands together briskly until dry.
- Children under 6 years of age should be supervised when using this product.

Other information

glycerin, hydrogen peroxide, purified water USP

Inactive ingredients

Purified Water (Aqua), Hydrogen Peroxide, Glycerol, Aloe, Fragrance

Questions or Comments?

Reach out to hello@compasscoffee.com 24/7

Package Label - Principal Display Panel

473ml NDC: 75333-001-02

473ml NDC: 75333-001-02

236ml NDC: 75333-001-01

236ml NDC: 75333-001-01

236ml NDC: 75333-002-01 236ml NDC: 75333-002-01

473ml NDC: 75333-002-02 236ml NDC: 75333-002-02